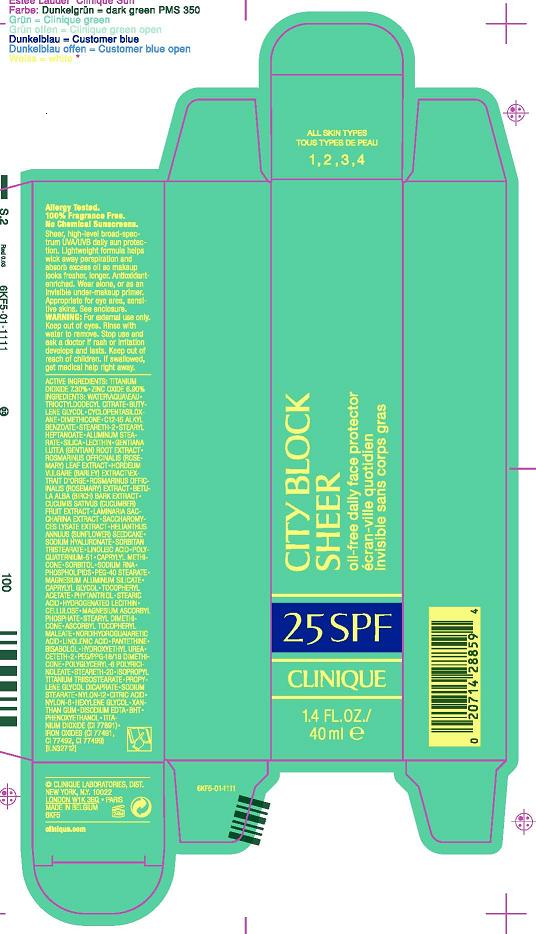 DRUG LABEL: CITY BLOCK SHEER
NDC: 49527-989 | Form: LOTION
Manufacturer: CLINIQUE LABORATORIES INC.
Category: otc | Type: HUMAN OTC DRUG LABEL
Date: 20100331

ACTIVE INGREDIENTS: TITANIUM DIOXIDE  7.30 mL/100 mL; ZINC OXIDE 6.9 mL/100 mL

ACTIVE INGREDIENT

ACTIVE INGREDIENTS: ZINC OXIDE 7.3%, TITANIUM DIOXIDE 6.9%

WARNINGS

WARNING: FOR EXTERNAL USE ONLY. KEEP OUT OF EYES. RINSE WITH WATER TO REMOVE. STOP USE AND ASK A DOCTOR IF RASH OR IRRITATION DEVELOPS AND LASTS. KEEP OUT OF REACH OF CHILDREN. IF SWALLOWED, GET MEDICAL HELP RIGHT AWAY.

PACKAGE LABEL

CLINIQUE CITY BLOCK SHEER SPF 25 OIL FREE FACE PROTECTOR

1.4 FL. OZ./ 40 mL

CLINIQUE LABORATORIES, DISTR.

NY, NY 10022

CLINIQUE.COM